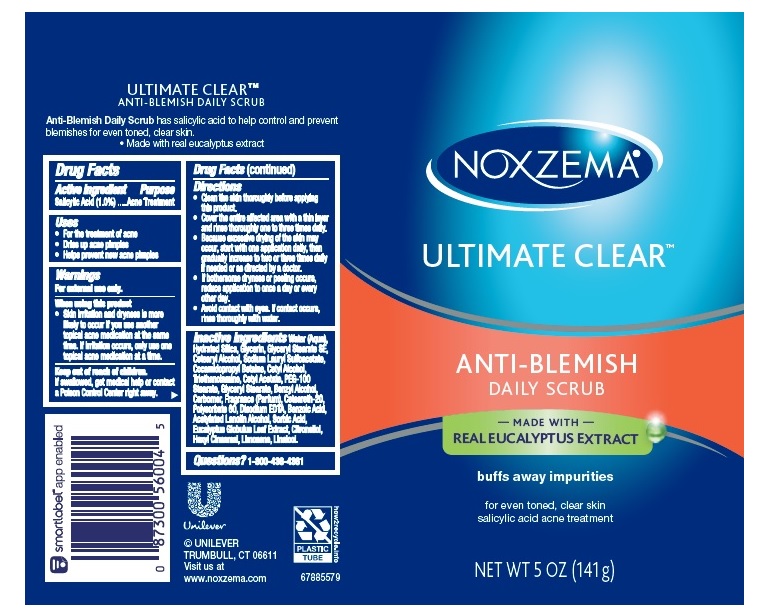 DRUG LABEL: Noxzema
NDC: 64942-1265 | Form: SOAP
Manufacturer: CONOPCO Inc. d/b/a Unilever
Category: otc | Type: HUMAN OTC DRUG LABEL
Date: 20241111

ACTIVE INGREDIENTS: SALICYLIC ACID 0.01 g/1 g
INACTIVE INGREDIENTS: EDETATE DISODIUM ANHYDROUS; EUCALYPTUS GLOBULUS LEAF; .BETA.-CITRONELLOL, (R)-; CETYL ALCOHOL; TROLAMINE; WATER; GLYCERIN; COCAMIDOPROPYL BETAINE; GLYCERYL STEARATE SE; CETOSTEARYL ALCOHOL; CETYL ACETATE; GLYCERYL MONOSTEARATE; PEG-100 STEARATE; SODIUM LAURYL SULFOACETATE; BENZYL ALCOHOL; CARBOXYPOLYMETHYLENE; BENZOIC ACID; ACETYLATED LANOLIN ALCOHOLS; SORBIC ACID; .ALPHA.-HEXYLCINNAMALDEHYDE; LIMONENE, (+)-; LINALOOL, (+/-)-; POLYOXYL 20 CETOSTEARYL ETHER; POLYSORBATE 60

Noxzema Ultimate Clear Anti-Blemish Daily Scrub

Drug Facts

Active ingredient
Salicylic Acid (1.0%)

Active ingredient

Salicylic Acid 1.0%

Purpose

Acne Treatment

Uses

- For the treatment of acne
- Dries up acne pimples
- Helps prevent new acne pimples

Warnings

For external use only
When using this product skin irritation and dryness is more likely to occur if you use another topical acne medication at the same time. If irritation occues, only use one topical acne medication at a time.

Keep out of reach of children.

If swallowed, get medical help or contact a Poison Control Center immediately.

Directions

- Clean the skin thoroughly before applying product
- Cover the entire affected area with a thin layer and rinse thoroughly one to three times daily
- Because excessive drying of the skin may occur, start with one application daily, then gradually increase to two or three times daily, if needed or as directed by a doctor.
- If bothersome dryness or peeling occurs, reduce application to once a day or every other day.

Avoid contact with eyes. If contact occurs, rinse thoroughly with water.

Inactive ingredients

Water (Aqua), Hydrated Silica, Glycerin, Glyceryl Stearate SE, Cetearyl Alcohol, Sodium Lauryl Sulfoacetate, Cocamidopropyl Betaine, Cetyl Alcohol, Triethanolamine, Cetyl Acetate, PEG-100 Stearate, Glyceryl Stearate, Benzyl Alcohol, Carbomer, Fragrance (Parfum), Ceteareth-20, Polysorbate 60, Disodium EDTA, Benzoic Acid, Acetylated Lanolin Alcohol, Sorbic Acid, Eucalyptus Globulus Leaf Extract, Citronellol, Hexyl Cinnamal, Limonene, Linalool.

Questions?

1-800-436-4361